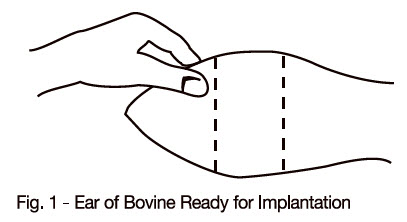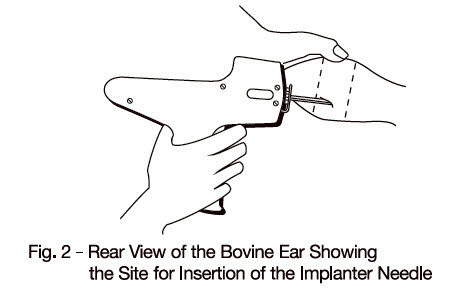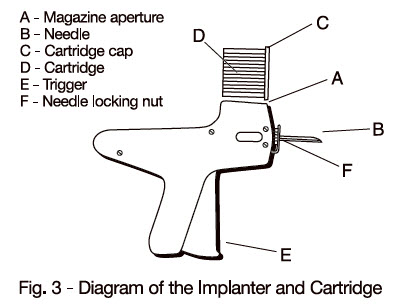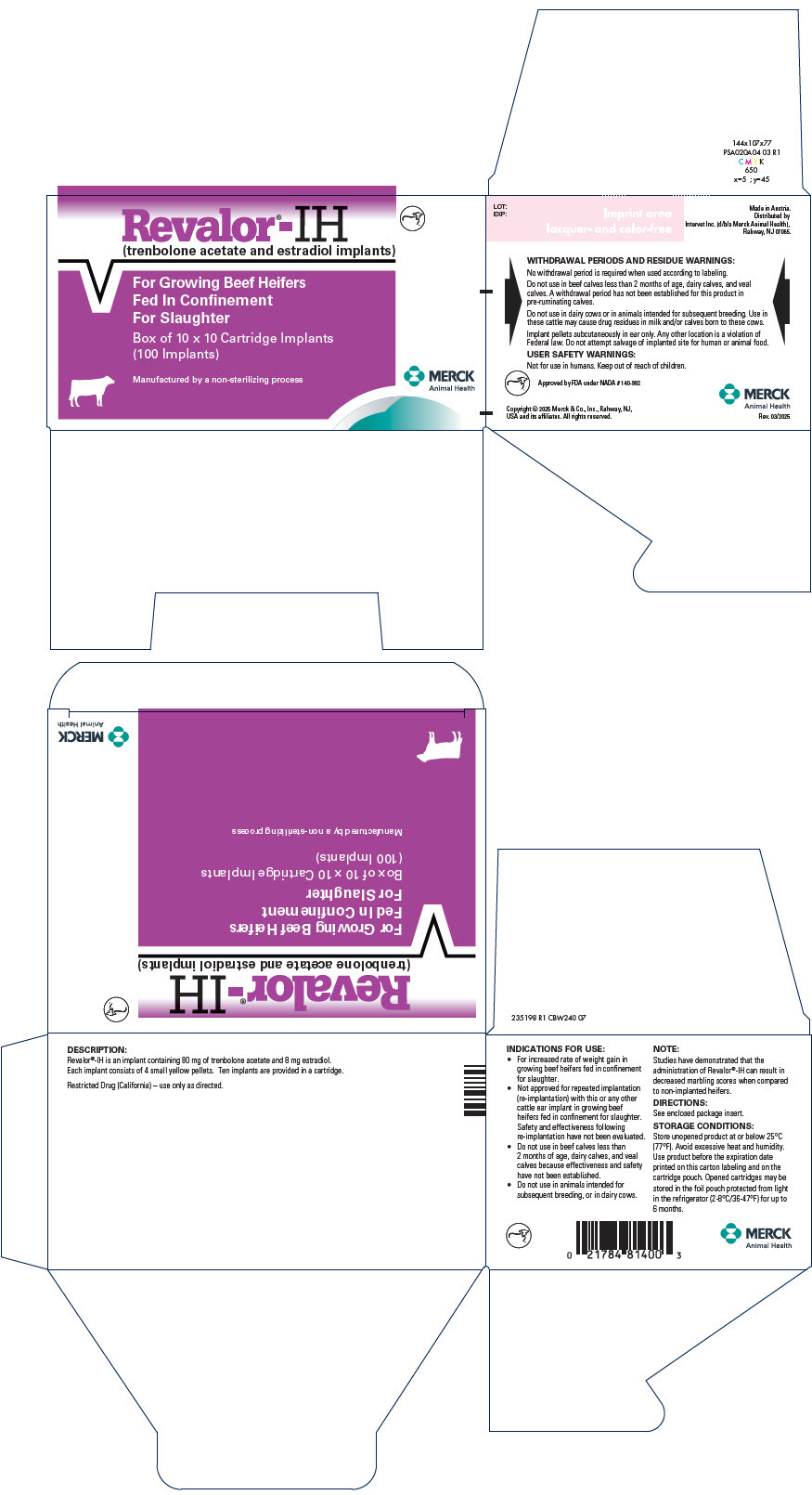 DRUG LABEL: Revalor-IH
NDC: 57926-025 | Form: IMPLANT
Manufacturer: Merck Sharp & Dohme Corp.
Category: animal | Type: OTC ANIMAL DRUG LABEL
Date: 20250929

ACTIVE INGREDIENTS: TRENBOLONE ACETATE 80 mg/1 1; ESTRADIOL 8 mg/1 1

Revalor®-IH
(trenbolone acetate and estradiol implants)

For Growing Beef Heifers
Fed In Confinement
For Slaughter

DESCRIPTION:

Revalor®-IH is an implant containing 80 mg of trenbolone acetate and 8 mg estradiol. Each implant consists of 4 small yellow pellets. Ten implants are provided in a cartridge.

Manufactured by a non-sterilizing process.

INDICATIONS FOR USE:

For increased rate of weight gain in growing beef heifers fed in confinement for slaughter.

Not approved for repeated implantation (re-implantation) with this or any other cattle ear implant in growing beef heifers fed in confinement for slaughter. Safety and effectiveness following re-implantation have not been evaluated.

Do not use in beef calves less than 2 months of age, dairy calves, and veal calves because effectiveness and safety have not been established.

Do not use in animals intended for subsequent breeding, or in dairy cows.

NOTE:

Studies have demonstrated that the administration of Revalor®-IH can result in decreased marbling scores when compared to non-implanted heifers.

DIRECTIONS:

The cartridge is designed to be used with a special implanting tool. The special implanting tool is available from Intervet Inc. Ten doses (implants) are in each cartridge. The implant is placed under the skin on the posterior aspect of the ear (see SITE OF IMPLANTATION and METHOD OF USE sections). See Page 2, DIRECTIONS for more detailed implantation directions.

With the animal suitably restrained, the skin on the outer surface of the ear should be cleaned. The implant is then administered by the method shown in the diagram below:

SITE OF IMPLANTATION:

After appropriately restraining the animal to allow access to the ear, cleanse the skin at the implant needle puncture site. It is subcutaneous between the skin and cartilage on the back side of the ear and below the midline of the ear. The implant must not be placed closer to the head than the edge of the cartilage ring farthest from the head. The location of insertion of the needle is a point toward the tip of the ear and at least a needle length away from the intended deposition site. Care should be taken to avoid injuring the major blood vessels or cartilage of the ear.

METHOD OF USE:

1. Do not remove the cap of the cartridge containing the implants.
2. Place the cartridge (D) with the capped end to the front into slot at the top of the implanter magazine marked (A) on the diagram.
3. Gently push the cartridge into the slot until it clicks into place.
4. The implanter is then ready for use.
5. Take the ear of the animal firmly with the free hand in the manner shown in Fig. 1. Then insert the needle into the subcutaneous tissue at the point indicated in Fig. 2 .
6. After inserting the needle to its full extent, squeeze the trigger (E) gradually. Allow the pellets of the implant to be deposited in a single row.
7. Withdraw the implanter. This will advance the cartridge one groove in the magazine and the next implant is now ready for use.
8. When all the implants have been administered, the cartridge will discharge out the bottom of the magazine and may be replaced by a new one.
9. To change the needle, loosen the needle locking nut labeled (F) in Fig. 3 and replace the needle. Tighten the nut finger tight and the implanter is ready for use.

WITHDRAWAL PERIODS AND RESIDUE WARNINGS:

No withdrawal period is required when used according to labeling.

Do not use in beef calves less than 2 months of age, dairy calves, and veal calves. A withdrawal period has not been established for this product in pre-ruminating calves.

Do not use in dairy cows or in animals intended for subsequent breeding. Use in these cattle may cause drug residues in milk and/or calves born to these cows.

Implant pellets subcutaneously in ear only. Any other location is a violation of Federal law. Do not attempt salvage of implanted site for human or animal food.

USER SAFETY WARNINGS:

Not for use in humans. Keep out of reach of children.

STORAGE CONDITIONS:

Store unopened product at or below 25°C (77°F). Avoid excessive heat and humidity. Use product before the expiration date printed on the carton labeling and on the cartridge pouch. Opened cartridges may be stored in the foil pouch protected from light in the refrigerator (2-8°C/36-47°F) for up to 6 months.

HOW SUPPLIED:

Box of 10 cartridges, each containing 10 implants per cartridge (100 implants total).

QUESTIONS/COMMENTS?

For a copy of the Safety Data Sheet or to report side effects, contact Merck Animal Health Technical Services at 1-800-211-3573. For additional information about reporting side effects for animal drugs, contact FDA at 1-888-FDA-VETS or http://www.fda.gov/reportanimalae

Made in Austria.

Distributed by
Intervet Inc. (d/b/a Merck Animal Health),
Rahway, NJ 07065.

Restricted Drug (California) – use only as directed.

Approved by FDA under NADA # 140-992

Copyright © 2025 Merck & Co., Inc., Rahway, NJ, USA and its affiliates.
All rights reserved.

MERCK
Animal Health

Rev. 03/2025

235196 R1

PRINCIPAL DISPLAY PANEL - 10 x 10 Cartridge Implant Carton

Revalor®-IH
(trenbolone acetate and estradiol implants)

For Growing Beef Heifers
Fed In Confinement
For Slaughter

Box of 10 x 10 Cartridge Implants
(100 implants)

Manufactured by a non-sterilizing process

MERCK
Animal Health